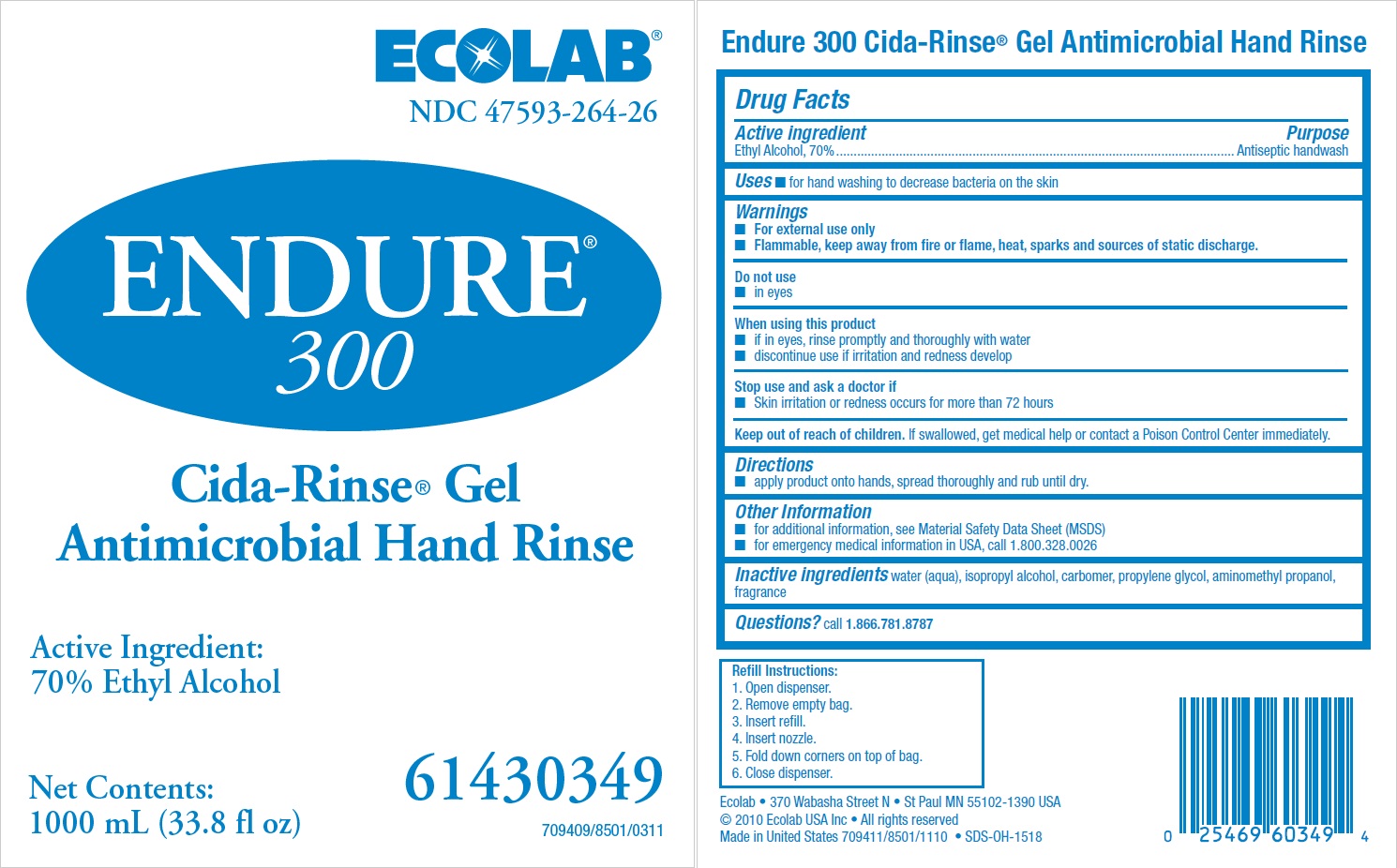 DRUG LABEL: Endure 300 Cida Rinse Gel
NDC: 47593-264 | Form: SOLUTION
Manufacturer: Ecolab Inc.
Category: otc | Type: HUMAN OTC DRUG LABEL
Date: 20240312

ACTIVE INGREDIENTS: ALCOHOL 70 mL/100 mL
INACTIVE INGREDIENTS: WATER; ISOPROPYL ALCOHOL; CARBOMER INTERPOLYMER TYPE A (ALLYL SUCROSE CROSSLINKED); PROPYLENE GLYCOL; AMINOMETHYLPROPANOL

Drug Facts

Active Ingredient

Ethyl Alcohol, 70%

Purpose

Antiseptic hand wash

Uses

- for hand washing to decrease bacteria on the skin

Warnings

- For external use only
- Flammable, keep away from fire or flame, heat, sparks and sources of static discharge.

Do not use

- in eyes

When using this product

- if in eyes, rinse promptly and thoroughly with water
- discontinue use if irritation and redness develop

Stop use and ask a doctor if

- Skin irritation or redness occurs for more than 72 hours

Keep out of reach of children. If swallowed, get medical help or contact a Poison Control Center immediately.

Directions

- apply product onto hands, spread thoroughly and rub until dry.

Other information

- for additional information, see Material Safety Data Sheet (MSDS)
- for emergency medical information in USA, call 1.800.328.0026

Inactive ingredients

water (aqua), isopropyl alcohol, carbomer, propylene glycol, aminomethyl propanol, fragrance

Questions? call 1.866.781.8787

Principal Display panel and representative label

Ecolab®

NDC 47593-264-26

Endure® 300

Cida-Rinse® Gel

Antimicrobial Hand Rinse

Active Ingredient:

70% Ethyl Alcohol

Net Contents:

1000 mL (33.8 fl oz)

61430349

709409/8501/0311

Ecolab • 370 Wabasha Street N • St Paul MN 55102-1390 USA

© 2010 Ecolab USA Inc • All rights reserved

Made in United States 709411/8501/1110 • SDS-OH-1518